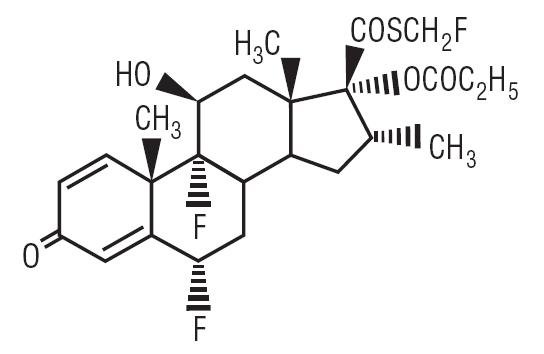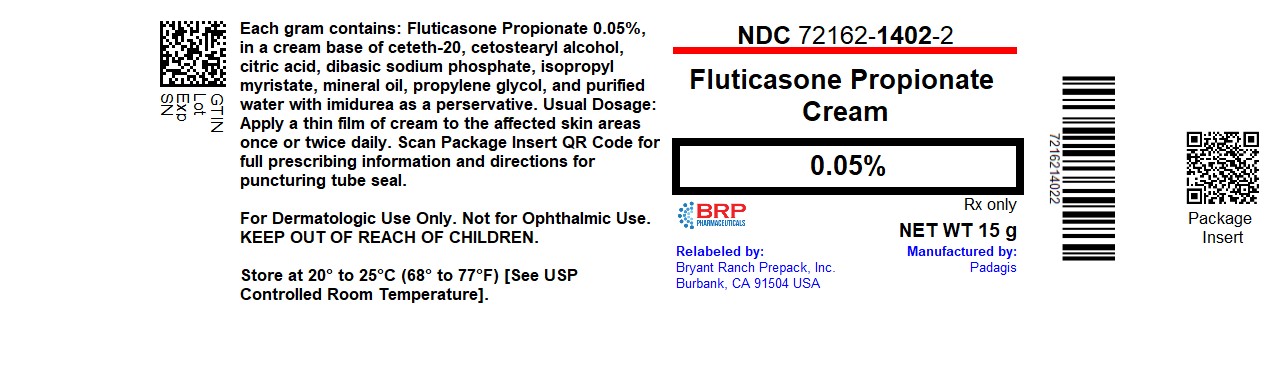 DRUG LABEL: Fluticasone Propionate
NDC: 72162-1402 | Form: CREAM
Manufacturer: Bryant Ranch Prepack
Category: prescription | Type: HUMAN PRESCRIPTION DRUG LABEL
Date: 20251030

ACTIVE INGREDIENTS: FLUTICASONE PROPIONATE 0.5 mg/1 g
INACTIVE INGREDIENTS: CETETH-20; CETOSTEARYL ALCOHOL; CITRIC ACID MONOHYDRATE; SODIUM PHOSPHATE, DIBASIC, UNSPECIFIED FORM; ISOPROPYL MYRISTATE; MINERAL OIL; PROPYLENE GLYCOL; WATER; IMIDUREA

Fluticasone Propionate Cream, 0.05%

For Dermatologic Use Only. Not for Ophthalmic Use.

Rx Only

DESCRIPTION

Fluticasone Propionate Cream, 0.05% contains fluticasone propionate [(6α,11β,16α,17α)-6,9,-difluoro-11-hydroxy-16-methyl-3-oxo-17-(1-oxopropoxy)androsta-1,4-diene-17-carbothioic acid, S-fluoromethyl ester], a synthetic fluorinated corticosteroid, for topical dermatologic use. The topical corticosteroids constitute a class of primarily synthetic steroids used as anti-inflammatory and antipruritic agents.

Chemically, fluticasone propionate is C25H31F3O5S. It has the following structural formula:

Fluticasone propionate has a molecular weight of 500.6. It is a white to off-white powder and is insoluble in water.

Each gram of Fluticasone Propionate Cream, 0.05% contains fluticasone propionate 0.5 mg in a base of ceteth-20, cetostearyl alcohol, citric acid, dibasic sodium phosphate, isopropyl myristate, mineral oil, propylene glycol, and purified water, with imidurea as a preservative.

CLINICAL PHARMACOLOGY

Like other topical corticosteroids, fluticasone propionate has anti-inflammatory, antipruritic, and vasoconstrictive properties. The mechanism of the anti-inflammatory activity of the topical steroids, in general, is unclear. However, corticosteroids are thought to act by the induction of phospholipase A2 inhibitory proteins, collectively called lipocortins. It is postulated that these proteins control the biosynthesis of potent mediators of inflammation such as prostaglandins and leukotrienes by inhibiting the release of their common precursor, arachidonic acid. Arachidonic acid is released from membrane phospholipids by phospholipase A2.

Fluticasone propionate is lipophilic and has a strong affinity for the glucocorticoid receptor. It has weak affinity for the progesterone receptor, and virtually no affinity for the mineralocorticoid, estrogen, or androgen receptors. The therapeutic potency of glucocorticoids is related to the half-life of the glucocorticoid-receptor complex. The half-life of the fluticasone propionate-glucocorticoid receptor complex is approximately 10 hours.

Studies performed with fluticasone propionate cream, 0.05% indicate that it is in the medium range of potency as compared with other topical corticosteroids.

Pharmacokinetics

Absorption -

The activity of Fluticasone Propionate Cream, 0.05% is due to the parent drug, fluticasone propionate. The extent of percutaneous absorption of topical corticosteroids is determined by many factors, including the vehicle and the integrity of the epidermal barrier. Occlusive dressing enhances penetration. Topical corticosteroids can be absorbed from normal intact skin. Inflammation and/or other disease processes in the skin increase percutaneous absorption.

In a human study of 12 healthy males receiving 12.5 g of 0.05% fluticasone propionate cream twice daily for 3 weeks, plasma levels were generally below the level of quantification (0.05 ng/mL). In another study of 6 healthy males administered 25 g of 0.05% fluticasone propionate cream under occlusion for 5 days, plasma levels of fluticasone ranged from 0.07 to 0.39 ng/mL.

In an animal study using radiolabeled 0.05% fluticasone propionate cream and ointment preparations, rats received a topical dose of 1 g/kg for a 24-hour period. Total recovery of radioactivity was approximately 80% at the end of 7 days. The majority of the dose (73%) was recovered from the surface of the application site. Less than 1% of the dose was recovered in the skin at the application site. Approximately 5% of the dose was absorbed systemically through the skin. Absorption from the skin continued for the duration of the study (7 days), indicating a long retention time at the application site.

Distribution -

Following intravenous administration of 1 mg fluticasone propionate in healthy volunteers, the initial disposition phase for fluticasone propionate was rapid and consistent with its high lipid solubility and tissue binding. The apparent volume of distribution averaged 4.2 L/kg (range, 2.3 to 16.7 L/kg). The percentage of fluticasone propionate bound to human plasma proteins averaged 91%. Fluticasone propionate is weakly and reversibly bound to erythrocytes. Fluticasone propionate is not significantly bound to human transcortin.

Metabolism -

No metabolites of fluticasone propionate were detected in an in vitro study of radiolabeled fluticasone propionate incubated in a human skin homogenate. The total blood clearance of systemically absorbed fluticasone propionate averages 1,093 mL/min (range, 618 to 1,702 mL/min) after a 1-mg intravenous dose, with renal clearance accounting for less than 0.02% of the total. Fluticasone propionate is metabolized in the liver by cytochrome P450 3A4-mediated hydrolysis of the 5-fluoromethyl carbothioate grouping. This transformation occurs in 1 metabolic step to produce the inactive 17-β-carboxylic acid metabolite, the only known metabolite detected in man. This metabolite has approximately 2,000 times less affinity than the parent drug for the glucocorticoid receptor of human lung cytosol in vitro and negligible pharmacological activity in animal studies. Other metabolites detected in vitro using cultured human hepatoma cells have not been detected in man.

Excretion -

Following intravenous dose of 1 mg in healthy volunteers, fluticasone propionate showed polyexponential kinetics and had an average terminal half-life of 7.2 hours (range, 3.2 to 11.2 hours).

INDICATIONS AND USAGE

Fluticasone Propionate Cream, 0.05% is a medium potency corticosteroid indicated for the relief of the inflammatory and pruritic manifestations of corticosteroid-responsive dermatoses. Fluticasone Propionate Cream, 0.05% may be used with caution in pediatric patients 3 months of age or older. The safety and efficacy of drug use for longer than 4 weeks in this population have not been established. The safety and efficacy of Fluticasone Propionate Cream, 0.05% in pediatric patients below 3 months of age have not been established.

CONTRAINDICATIONS

Fluticasone Propionate Cream, 0.05% is contraindicated in those patients with a history of hypersensitivity to any of the components in the preparation (see PRECAUTIONS).

PRECAUTIONS

Fluticasone Propionate Cream, 0.05% contains the excipient imidurea which releases formaldehyde as a breakdown product. Formaldehyde may cause allergic sensitization or irritation upon contact with the skin. Fluticasone Propionate Cream, 0.05% should not be used in individuals with hypersensitivity to formaldehyde as it may prevent healing or worsen dermatitis.

General -

Systemic absorption of topical corticosteroids can produce reversible hypothalamic-pituitary-adrenal (HPA) axis suppression with the potential for glucocorticosteroid insufficiency after withdrawal from treatment. Manifestations of Cushing's syndrome, hyperglycemia, and glucosuria can also be produced in some patients by systemic absorption of topical corticosteroids while on treatment.

Patients applying a potent topical steroid to a large surface area or to areas under occlusion should be evaluated periodically for evidence of HPA axis suppression. This may be done by using the ACTH stimulation, A.M. plasma cortisol, and urinary free cortisol tests.

If HPA axis suppression is noted, an attempt should be made to withdraw the drug, to reduce the frequency of application, or to substitute a less potent steroid. Recovery of HPA axis function is generally prompt upon discontinuation of topical corticosteroids. Infrequently, signs and symptoms of glucocorticosteroid insufficiency may occur requiring supplemental systemic corticosteroids. For information on systemic supplementation, see prescribing information for those products.

Fluticasone propionate cream, 0.05% caused depression of A.M. plasma cortisol levels in 1 of 6 adult patients when used daily for 7 days in patients with psoriasis or eczema involving at least 30% of the body surface. After 2 days of treatment, this patient developed a 60% decrease from pretreatment values in the A.M. plasma cortisol level.

There was some evidence of corresponding decrease in the 24-hour urinary free cortisol levels. The A.M. plasma cortisol level remained slightly depressed for 48 hours but recovered by day 6 of treatment.

Fluticasone propionate cream, 0.05%, caused HPA axis suppression in 2 of 43 pediatric patients, ages 2 and 5 years old, who were treated for 4 weeks covering at least 35% of the body surface area. Follow-up testing 12 days after treatment discontinuation, available for 1 of the 2 subjects, demonstrated a normally responsive HPA axis (see PRECAUTIONS - Pediatric Use).

Pediatric patients may be more susceptible to systemic toxicity from equivalent doses due to their larger skin surface to body mass ratios (see PRECAUTIONS - Pediatric Use).

The following local adverse reactions have been reported with topical corticosteroids, and they may occur more frequently with the use of occlusive dressings and higher potency corticosteroids. These reactions are listed in an approximately decreasing order of occurrence: irritation, folliculitis, acneiform eruptions, hypopigmentation, perioral dermatitis, allergic contact dermatitis, secondary infections, skin atrophy, striae, hypertrichosis, and miliaria.

Fluticasone Propionate Cream, 0.05% may cause local cutaneous adverse reactions (see ADVERSE REACTIONS).

If irritation develops, Fluticasone Propionate Cream, 0.05% should be discontinued and appropriate therapy instituted. Allergic contact dermatitis with corticosteroids is usually diagnosed by observing failure to heal rather than noting a clinical exacerbation as with most topical products not containing corticosteroids. Such an observation should be corroborated with appropriate diagnostic patch testing.

If concomitant skin infections are present or develop, an appropriate antifungal or antibacterial agent should be used. If a favorable response does not occur promptly, use of Fluticasone Propionate Cream, 0.05% should be discontinued until the infection has been adequately controlled.

Fluticasone Propionate Cream, 0.05% should not be used in the presence of preexisting skin atrophy and should not be used where infection is present at the treatment site. Fluticasone Propionate Cream, 0.05% should not be used in the treatment of rosacea and perioral dermatitis.

Information for Patients -

Patients using topical corticosteroids should receive the following information and instructions:

1. This medication is to be used as directed by the physician. It is for external use only. Avoid contact with the eyes.
2. This medication should not be used for any disorder other than that for which it was prescribed.
3. The treated skin area should not be bandaged or otherwise covered or wrapped so as to be occlusive unless directed by the physician.
4. Patients should report to their physician any signs of local adverse reactions as well as non-healing or worsening of skin condition.
5. Parents of pediatric patients should be advised not to use this medication in the treatment of diaper dermatitis. Fluticasone Propionate Cream, 0.05% should not be applied in the diaper areas as diapers or plastic pants may constitute occlusive dressing (see DOSAGE AND ADMINISTRATION).
6. This medication should not be used on the face, underarms, or groin areas unless directed by a physician.
7. As with other corticosteroids, therapy should be discontinued when control is achieved. If no improvement is seen within 2 weeks, contact the physician.
8. Patients should report to their physician if they are allergic to formaldehyde.

Laboratory Tests -

The following tests may be helpful in evaluating patients for HPA axis suppression:

ACTH stimulation test

A.M. plasma cortisol test

Urinary free cortisol test

Carcinogenesis, Mutagenesis, Impairment of Fertility -

Two 18-month studies were performed in mice to evaluate the carcinogenic potential of fluticasone propionate when given topically (as an 0.05% ointment) and orally. No evidence of carcinogenicity was found in either study.

Fluticasone propionate was not mutagenic in the standard Ames test, E. coli fluctuation test, S. cerevisiae gene conversion test, or Chinese Hamster ovarian cell assay. It was not clastogenic in mouse micronucleus or cultured human lymphocyte tests.

In a fertility and general reproductive performance study in rats, fluticasone propionate administered subcutaneously to females at up to 50 mcg/kg per day and to males at up to 100 mcg/kg per day (later reduced to 50 mcg/kg per day) had no effect upon mating performance or fertility. These doses are approximately 15 and 30 times, respectively, the human systemic exposure following use of the recommended human topical dose of fluticasone propionate cream, 0.05%, assuming human percutaneous absorption of approximately 3% and the use in a 70-kg person of 15 g/day.

Pregnancy:

Teratogenic Effects:

Pregnancy Category C -

Corticosteroids have been shown to be teratogenic in laboratory animals when administered systemically at relatively low dosage levels. Some corticosteroids have been shown to be teratogenic after dermal application in laboratory animals. Teratology studies in the mouse demonstrated fluticasone propionate to be teratogenic (cleft palate) when administered subcutaneously in doses of 45 mcg/kg/day and 150 mcg/kg/day. This dose is approximately 14 and 45 times, respectively, the human topical dose of fluticasone propionate cream, 0.05%. There are no adequate and well-controlled studies in pregnant women. Fluticasone Propionate Cream, 0.05%, should be used during pregnancy only if the potential benefit justifies the potential risk to the fetus.

Nursing Mothers -

Systemically administered corticosteroids appear in human milk and could suppress growth, interfere with endogenous corticosteroid production, or cause other untoward effects. It is not known whether topical administration of corticosteroids could result in sufficient systemic absorption to produce detectable quantities in human milk. Because many drugs are excreted in human milk, caution should be exercised when Fluticasone Propionate Cream, 0.05% is administered to a nursing woman.

Pediatric Use -

Fluticasone Propionate Cream, 0.05% contains the excipient imidurea which releases formaldehyde as a breakdown product. Formaldehyde may cause allergic sensitization or irritation upon contact with the skin. Fluticasone Propionate Cream, 0.05% should not be used in individuals with hypersensitivity to formaldehyde as it may prevent healing or worsen dermatitis.

Fluticasone Propionate Cream, 0.05% should be discontinued if control is achieved before 4 weeks. If no improvement is seen within 2 weeks, contact a physician. The safety and efficacy of drug use for longer than 4 weeks in this population have not been established.

The safety and efficacy of Fluticasone Propionate Cream, 0.05% in pediatric patients below 3 months of age have not been established.

Parents of pediatric patients should be advised not to use this medication in the treatment of diaper dermatitis unless directed by the physician. Fluticasone Propionate Cream, 0.05% should not be applied in the diaper areas as diapers or plastic pants may constitute occlusive dressing.

Fluticasone propionate cream, 0.05% caused HPA axis suppression in 2 of 43 pediatric patients, ages 2 and 5 years old, who were treated for 4 weeks covering at least 35% of the body surface area. Follow-up testing 12 days after treatment discontinuation, available for 1 of the 2 subjects, demonstrated a normally responsive HPA axis (see ADVERSE REACTIONS). Adverse effects including striae have been reported with use of topical corticosteroids in pediatric patients.

HPA axis suppression, Cushing's syndrome, linear growth retardation, delayed weight gain, and intracranial hypertension have been reported in pediatric patients receiving topical corticosteroids. Manifestations of adrenal suppression in pediatric patients include low plasma cortisol levels to an absence of response to ACTH stimulation. Manifestations of intracranial hypertension include bulging fontanelles, headaches, and bilateral papilledema. Administration of topical corticosteroids to children should be limited to the least amount compatible with an effective therapeutic regimen. Chronic corticosteroid therapy may interfere with the growth and development of children.

Geriatric Use -

A limited number of patients above 65 years of age (n=126) have been treated with fluticasone propionate cream, 0.05% in US and non-US clinical trials. While the number of patients is too small to permit separate analysis of efficacy and safety, the adverse reactions reported in this population were similar to those reported by younger patients. Based on available data, no adjustment of dosage of Fluticasone Propionate Cream, 0.05% in geriatric patients is warranted.

ADVERSE REACTIONS

Clinical Trial Experience -

In controlled clinical trials of twice-daily administration, the total incidence of adverse reactions associated with the use of fluticasone propionate cream, 0.05% was approximately 4%. These adverse reactions were usually mild; self-limiting; and consisted primarily of pruritus, dryness, numbness of fingers, and burning. These events occurred in 2.9%, 1.2%, 1.0%, and 0.6% of patients, respectively.

Two clinical studies compared once- to twice-daily administration of fluticasone propionate cream, 0.05% for the treatment of moderate to severe eczema. The local drug-related adverse events for the 491 patients enrolled in both studies are shown in Table 1. In the study enrolling both adult and pediatric patients, the incidence of local adverse events in the 119 pediatric patients ages 1 to 12 years was comparable to the 140 patients ages 13 to 62 years.

Fifty-one pediatric patients ages 3 months to 5 years, with moderate to severe eczema, were enrolled in an open-label HPA axis safety study. Fluticasone propionate cream, 0.05% was applied twice daily for 3 to 4 weeks over an arithmetic mean body surface area of 64% (range, 35% to 95%). The mean morning cortisol levels with standard deviations before treatment (prestimulation mean value = 13.76 ± 6.94 mcg/dL, poststimulation mean value = 30.53 ± 7.23 mcg/dL) and at end treatment (prestimulation mean value = 12.32 ± 6.92 mcg/dL, poststimulation mean value = 28.84 ± 7.16 mcg/dL) showed little change. In 2 of 43 (4.7%) patients with end-treatment results, peak cortisol levels following cosyntropin stimulation testing were ≤18 μg/dL, indicating adrenal suppression. Follow-up testing after treatment discontinuation, available for 1 of the 2 subjects, demonstrated a normally responsive HPA axis. Local drug-related adverse events were transient burning, resolving the same day it was reported; transient urticaria, resolving the same day it was reported; erythematous rash; dusky erythema, resolving within 1 month after cessation of fluticasone propionate cream, 0.05%; and telangiectasia, resolving within 3 months after stopping fluticasone propionate cream, 0.05%.

Table 1: Drug-Related Adverse Events-Skin
Adverse Events | Fluticasone Once Daily (n = 210) | Fluticasone Twice Daily (n = 203) | Vehicle Twice Daily; (n = 78)
Skin infection; Infected eczema; Viral warts; Herpes simplex; Impetigo; Atopic dermatitis; Eczema; Exacerbation of eczema; Erythema; Burning; Stinging; Skin irritation; Pruritus; Exacerbation of pruritus; Folliculitis; Blisters; Dryness of skin | 1 (0.5%); 1 (0.5%); 0; 0; 1 (0.5%); 1 (0.5%); 1 (0.5%); 4 (1.9%); 0; 2 (1.0%); 0; 6 (2.9%); 2 (1.0%); 4 (1.9%); 1 (0.5%); 0; 3 (1.4%) | 0; 2 (1.0%); 1 (0.5%); 1 (0.5%); 0; 0; 0; 1 (0.5%); 2 (1.0%); 2 (1.0%); 2 (1.0%); 2 (1.0%); 4. (1.9%); 1 (0.5%); 1 (0.5%); 1 (0.5%); 1 (0.5%) | 0; 0; 0; 0; 0; 0; 0; 1 (1.3%); 0; 2 (2.6%); 1 (1.3%); 0; 4 (5.1%); 1 (1.3%); 0; 0; 0

Table 2: Adverse Events* From Pediatric Open-Label Trial (n=51)
Adverse Events | Fluticasone Twice Daily
Burning; Dusky erythema; Erythematous rash; Facial telangiectasia†; Non-facial telangiectasia; Urticaria | 1 (2.0%); 1 (2.0%); 1 (2.0%); 2 (4.9%); 1 (2.0%); 1 (2.0%)
* See text for additional detail.
† n=41.

Post Marketing Experience -

Systemic adverse events with fluticasone propionate cream, 0.05% and fluticasone propionate ointment have included: immunosuppression/Pneumocystis carinii pneumonia/leukopenia/thrombocytopenia; hyperglycemia/glycosuria; Cushing’s syndrome; generalized body edema/blurred vision; and acute urticarial reaction (edema, urticaria, pruritus, and throat swelling).

The following localized adverse reactions have been reported during post approval use of fluticasone propionate cream, 0.05%: skin discoloration, erythema, irritation, edema/swelling, atrophy, contusion, dermatitis, pain, sepsis, hemorrhage, acneiform eruptions.

Because these reactions are reported voluntarily from a population of uncertain size, it is not always possible to reliably estimate their frequency or establish a causal relationship to drug exposure.

OVERDOSAGE

Topically applied Fluticasone Propionate Cream, 0.05% can be absorbed in sufficient amounts to produce systemic effects (see PRECAUTIONS).

DOSAGE AND ADMINISTRATION

Fluticasone Propionate Cream, 0.05% may be used in adult and pediatric patients 3 months of age or older. Safety and efficacy of Fluticasone Propionate Cream, 0.05% in pediatric patients for more than 4 weeks of use have not been established (see PRECAUTIONS - Pediatric Use). The safety and efficacy of Fluticasone Propionate Cream, 0.05% in pediatric patients below 3 months of age have not been established.

Atopic Dermatitis -

Apply a thin film of Fluticasone Propionate Cream, 0.05% to the affected skin areas once or twice daily. Rub in gently.

Other Corticosteroid-Responsive Dermatoses -

Apply a thin film of Fluticasone Propionate Cream, 0.05% to the affected skin areas twice daily. Rub in gently.

As with other corticosteroids, therapy should be discontinued when control is achieved. If no improvement is seen within 2 weeks, reassessment of diagnosis may be necessary.

Fluticasone Propionate Cream, 0.05% should not be used with occlusive dressings. Fluticasone Propionate Cream, 0.05% should not be applied in the diaper area, as diapers or plastic pants may constitute occlusive dressings.

Geriatric Use -

In studies where geriatric patients (65 years of age or older, see PRECAUTIONS) have been treated with fluticasone propionate cream, 0.05%, safety did not differ from that in younger patients; therefore, no dosage adjustment is recommended.

CLINICAL STUDIES

Psoriasis Studies -

In 2 vehicle-controlled studies, fluticasone propionate cream, 0.05% applied twice daily was significantly more effective than the vehicle in the treatment of moderate to severe psoriasis. The investigator's global evaluation after 28 days of treatment is shown in Table 3.

Table 3: Physician’s Assessment of Clinical Response
 | Fluticasone propionate cream, 0.05% |  | Vehicle
 | Study 1; (n = 59) | Study 2; (n = 74) | Study 1; (n = 66) | Study 2; (n = 75)
Cleared; Excellent; Good; Fair; Poor; Worse | 8%; 29%; 27%; 27%; 7%; 2% | 1%; 28%; 34%; 15%; 22%; 0 | 3%; 11%; 20%; 33%; 24%; 9% | 1%; 17%; 28%; 25%; 27%; 1%

The clinical signs of psoriasis were scored on a scale of 0=absent, 1=mild, 2=moderate, and 3=severe. The mean improvements over baseline in the clinical signs at the end of treatment are shown in Table 4.

Table 4: Clinical Signs: Mean Improvements Over Baseline
 | Fluticasone propionate cream, 0.05% |  | Vehicle
 | Study 1 | Study 2 | Study 1 | Study 2
Erythema; Thickening; Scaling | 1.19; 1.22; 1.53 | 1.07; 1.17; 1.39 | 0.55; 0.81; 0.95 | 0.84; 0.97; 1.21

Atopic Dermatitis Studies -

In 2 controlled 28-day studies, fluticasone propionate cream, 0.05% once daily was equivalent to fluticasone propionate cream, 0.05% twice daily in the treatment of moderate to severe eczema. The investigator's global evaluation after 28 days of treatment is shown in Table 5.

Table 5: Physician’s Assessment of Clinical Response
 | Fluticasone propionate cream, 0.05%, Once Daily |  | Fluticasone propionate cream, 0.05%, Twice Daily
 | Study 1; (n = 64) | Study 2; (n = 106) | Study 1; (n = 65) | Study 2; (n = 100)
Cleared; Excellent; Good; Fair; Poor; Worse | 30%; 42%; 17%; 3%; 5%; 3% | 20%; 32%; 26%; 14%; 3%; 6% | 48%; 32%; 5%; 6%; 8%; 2% | 21%; 50%; 12%; 10%; 4%; 3%

The clinical signs and symptoms of atopic dermatitis were scored on a scale of 0=absent, 1=mild, 2=moderate, and 3=severe. The mean improvements over baseline at the end of treatment are shown in Table 6.

Table 6: Clinical Signs and Symptoms: Mean Improvements Over Baseline
 | Fluticasone propionate cream, 0.05%, Once Daily |  | Fluticasone propionate cream, 0.05%, Twice Daily
 | Study 1 | Study 2 | Study 1 | Study 2
Erythema; Pruritus; Thickening; Lichenification; Vesiculation; Crusting | 1.7; 2.1; 1.6; 1.2; 0.5; 0.6 | 1.5; 1.6; 1.3; 1.2; 0.4; 0.7 | 1.8; 2.1; 1.6; 1.2; 0.5; 0.8 | 1.7; 1.7; 1.5; 1.3; 0.5; 0.8

HOW SUPPLIED

Fluticasone Propionate Cream, 0.05% is available as follows:

15 g tube (NDC 72162-1402-2)

30 g tube (NDC 72162-1402-3)

60 g tube (NDC 72162-1402-6)

Repackaged/Relabeled by:
Bryant Ranch Prepack, Inc. Burbank, CA 91504

STORAGE

Store at 20-25°C (68-77°F) [see USP Controlled Room Temperature].

Manufactured by Perrigo

Bronx, NY 10457

Distributed By

Perrigo®

Allegan, MI 49010

www.perrigo.com

Rev 05-15

: 1H300 RC JX1

PACKAGE LABEL

Fluticasone Propionate 0.05% Cream